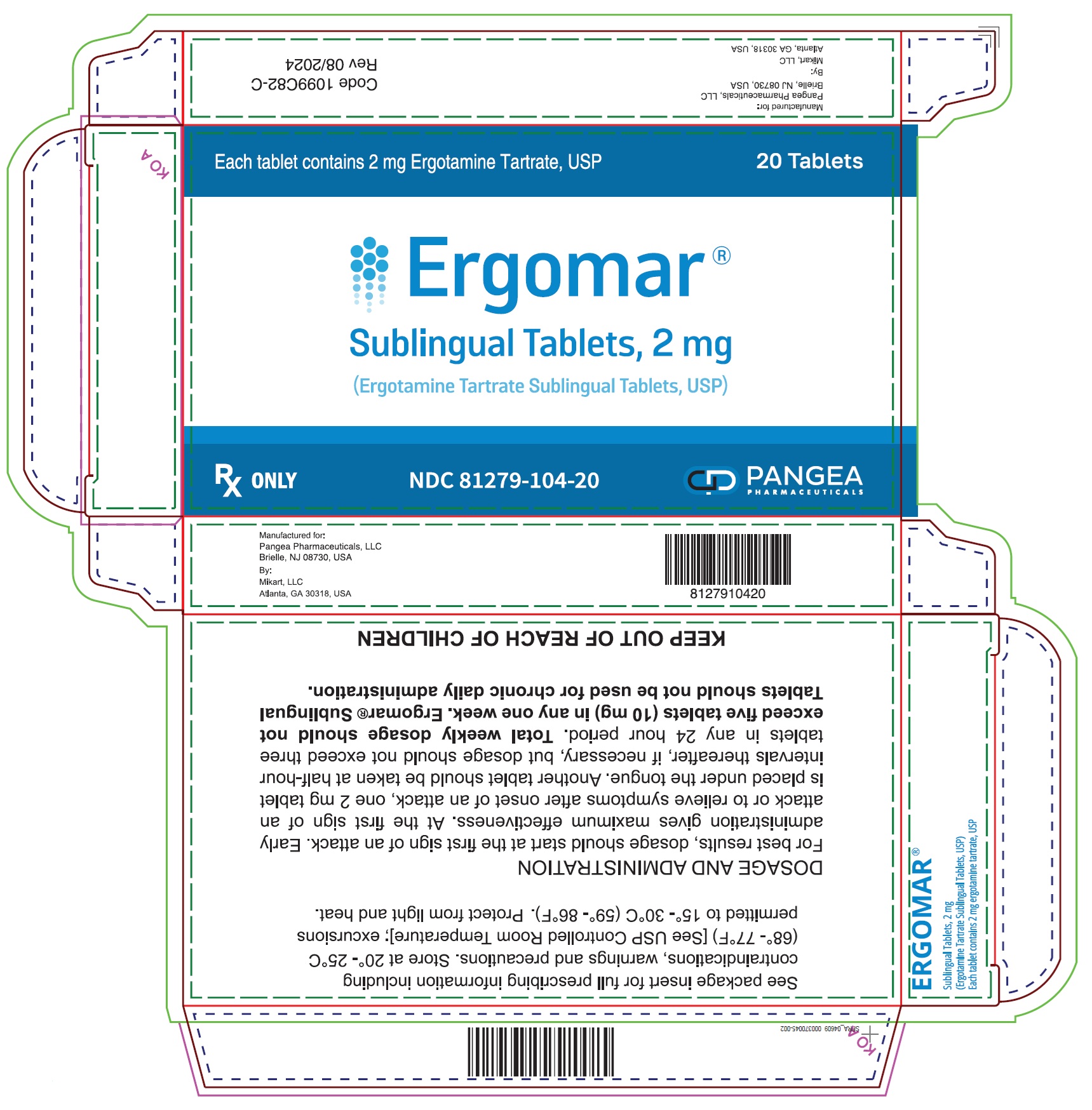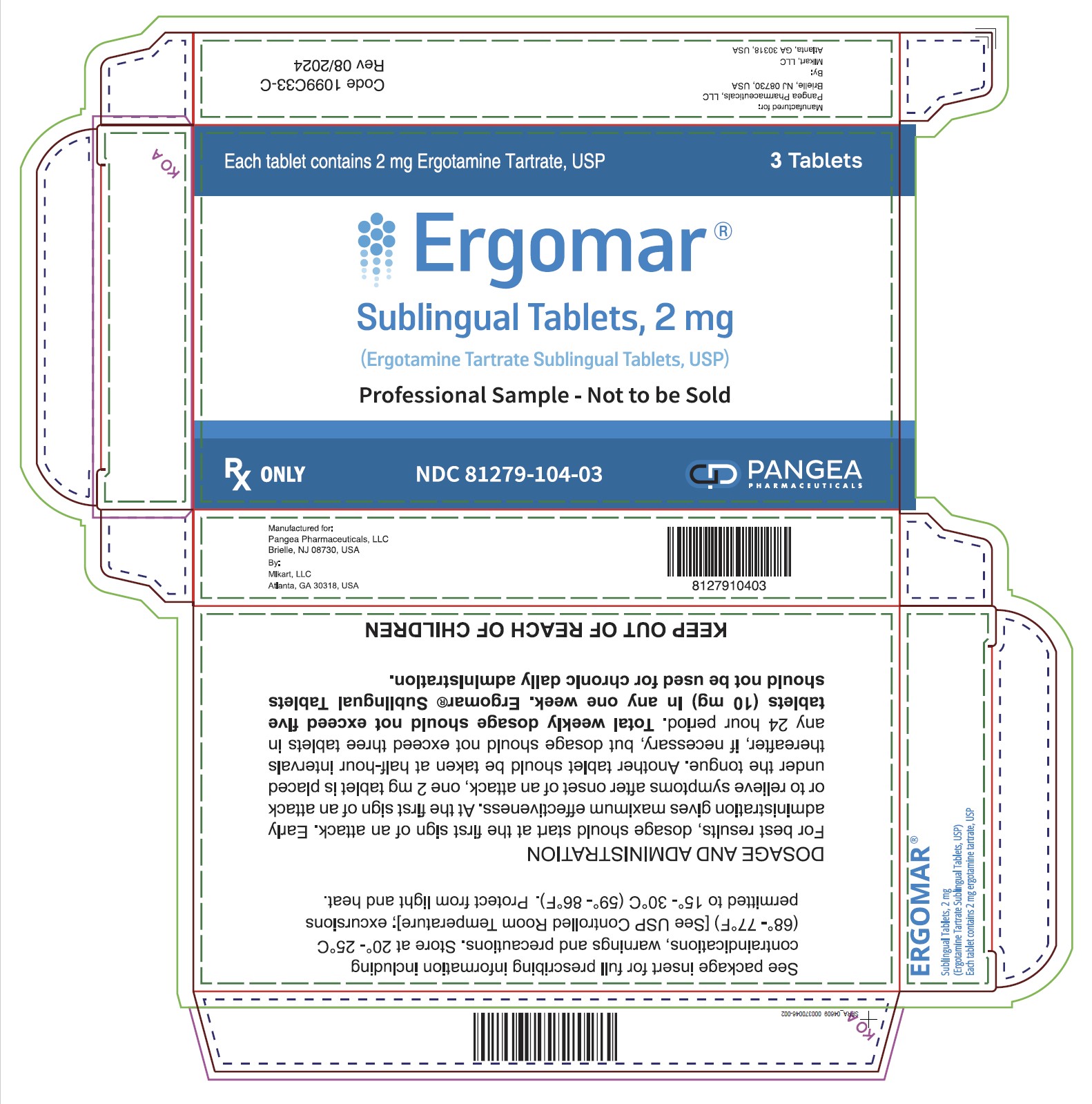 DRUG LABEL: Ergomar 


NDC: 81279-104 | Form: TABLET
Manufacturer: Pangea Pharmaceuticals LLC
Category: prescription | Type: HUMAN PRESCRIPTION DRUG LABEL
Date: 20250225

ACTIVE INGREDIENTS: ERGOTAMINE TARTRATE 2 mg/1 1
INACTIVE INGREDIENTS: MICROCRYSTALLINE CELLULOSE; CROSPOVIDONE; SACCHARIN SODIUM; MAGNESIUM STEARATE; FD&C BLUE NO. 1; ALUMINUM OXIDE; D&C YELLOW NO. 10

Ergomar®Sublingual Tablets, 2 mg

(Ergotamine Tartrate Sublingual Tablets, USP)

Rx Only

WARNING

Serious and/or life-threatening peripheral ischemia has been associated with the coadministration of ergotamine tartrate with potent CYP 3A4 inhibitors including protease inhibitors and macrolide antibiotics. Because CYP 3A4 inhibition elevates the serum levels of ergotamine tartrate, the risk for vasospasm leading to cerebral ischemia and/or ischemia of the extremities is increased. Hence, concomitant use of these medications is contraindicated. (See also CONTRAINDICATIONSand WARNINGSsection)

DESCRIPTION:

Ergomar®Sublingual Tablets

Ergotamine Tartrate Sublingual Tablets USP ... 2 mg

Inactive Ingredients:Microcrystalline Cellulose NF, Natural Peppermint Flavor Powder, Crospovidone NF, Saccharin Sodium USP Powder, D&C Yellow #10 Lake, Magnesium Stearate NF, FD&C Blue #1 Aluminum Lake.

CLINICAL PHARMACOLOGY:

Ergotamine is an alpha adrenergic blocking agent with a direct stimulating effect on the smooth muscle of peripheral and cranial blood vessels and produces depression of central vasomotor centers. The compound also has the properties of serotonin antagonism. In comparison to hydrogenated ergotamine, the adrenergic blocking actions are less pronounced and vasoconstrictive actions are greater.

Pharmacokinetics: Interactions

Pharmacokinetic interactions (increased blood levels of ergotamine) have been reported in patients treated orally with ergotamine and macrolide antibiotics (e.g., troleandomycin, clarithromycin, erythromycin), and in patients treated orally with ergotamine and protease inhibitors (e.g., ritonavir) presumably due to inhibition of cytochrome P450 3A metabolism of ergotamine (See CONTRAINDICATIONS). Ergotamine has also been shown to be an inhibitor of cytochrome P450 3A catalyzed reactions. No pharmacokinetic interactions involving other cytochrome P450 isoenzymes are known.

INDICATIONS AND USAGE

Ergomar®is indicated as therapy to abort or prevent vascular headache, e.g., migraine, migraine variants or so-called "histaminic cephalalgia".

CONTRAINDICATIONS

Coadministration of ergotamine with potent CYP 3A4 inhibitors (ritonavir, nelfinavir, indinavir, erythromycin, clarithromycin and troleandomycin) has been associated with acute ergot toxicity (ergotism) characterized by vasospasm and ischemia of the extremities (See PRECAUTIONS: Drug Interactions), with some cases resulting in amputation. There have been rare reports of cerebral ischemia in patients on protease inhibitor therapy when ergotamine was coadministered, at least one resulting in death. Because of the increased risk for ergotism and other serious vasospastic adverse events, ergotamine use is contraindicated with these drugs and other potent inhibitors of CYP 3A4 (e.g., ketoconazole, itraconazole) (See WARNINGS: CYP 3A4 Inhibitors).

Ergomar®Sublingual Tablets may cause fetal harm when administered to pregnant women. Ergomar®Sublingual Tablets are contraindicated in women who are or may become pregnant. If this drug is used during pregnancy or if the patient becomes pregnant while taking this product, the patient should be apprised of the potential hazard to the fetus. Peripheral vascular disease, coronary heart disease, hypertension, impaired hepatic or renal function and sepsis.

Hypersensitivity to any of the components.

WARNINGS

CYP 3A4 Inhibitors (e.g., Macrolide Antibiotics and Protease Inhibitors)

Coadministration of ergotamine with potent CYP 3A4 inhibitors such as protease inhibitors or macrolide antibiotics has been associated with serious adverse events; for this reason, these drugs should not be given concomitantly with ergotamine (See CONTRAINDICATIONS). While these reactions have not been reported with less potent CYP 3A4 inhibitors, there is a potential risk for serious toxicity including vasospasm when these drugs are used with ergotamine. Examples of less potent CYP 3A4 inhibitors include: saquinavir, nefazodone, fluconazole, fluoxetine, grapefruit juice, fluvoxamine, zileuton, metronidazole, and clotrimazole. These lists are not exhaustive, and the prescriber should consider the effects on CYP 3A4 of other agents being considered for concomitant use with ergotamine.

Fibrotic Complications

There have been a few reports of patients on ergotamine tartrate and caffeine therapy developing retroperitoneal and/or pleuropulmonary fibrosis. There have also been rare reports of fibrotic thickening of the aortic, mitral, tricuspid, and/or pulmonary valves with long-term continuous use of ergotamine tartrate and caffeine. Ergomar®Sublingual Tablets should not be used for chronic daily administration (See DOSAGE AND ADMINISTRATION).

PRECAUTIONS

General

Although signs and symptoms of ergotism rarely develop even after long term intermittent use of the drug, care should be exercised to remain within the limits of recommended dosage. Ergotism is manifested by intense arterial vasoconstriction, producing signs and symptoms of peripheral vascular ischemia. Ergotamine induces vasoconstriction by a direct action on vascular smooth muscle. In chronic intoxication with ergot derivatives, headache, intermittent claudication, muscle pains, numbness, coldness and pallor of the digits may occur. If the condition is allowed to progress untreated, gangrene can result. While most cases of ergotism associated with ergotamine treatment result from frank overdosage, some cases have involved apparent hypersensitivity. There are few reports of ergotism among patients taking doses within the recommended limits or for brief periods of time. In rare instances, patients, particularly those who have used the medication indiscriminately over long periods of time, may display withdrawal symptoms consisting of rebound headache upon discontinuation of the drug.

Information for Patients

Patients should be advised that one Ergomar®Sublingual Tablet should be taken at the first sign of a migraine headache. No more than 2 tablets should be taken for any single migraine attack. No more than 5 tablets should be taken during any 7-day period. Administration of Ergomar®Sublingual Tablets should not exceed the dosing guidelines and should not be used for chronic daily administration (See DOSAGE AND ADMINISTRATION). Ergomar®Sublingual Tablets should be used only for migraine headaches. It is not effective for other types of headaches and it lacks analgesic properties. Patients should be advised to report to the physician immediately any of the following: numbness or tingling in the fingers and toes, muscle pain in the arms and legs, weakness in the legs, pain in the chest or temporary speeding or slowing of the heart rate, swelling or itching.

Drug Interactions

CYP 3A4 Inhibitors (e.g., Macrolide Antibiotics and Protease inhibitors)

See CONTRAINDICATIONSand WARNINGS.

Ergomar®Sublingual Tablets (Ergotamine Tartrate Sublingual Tablets USP) should not be administered with other vasoconstrictors. Use with sympathomimetics (pressor agents) may cause extreme elevation of blood pressure. The beta-blocker Inderal (propranolol) has been reported to potentiate the vasoconstrictive action of ergotamine by blocking the vasodilating property of epinephrine. Nicotine may provoke vasoconstriction in some patients, predisposing to a greater ischemic response to ergot therapy. The blood levels of ergotamine-containing drugs are reported to be elevated by the concomitant administration of macrolide antibiotics and vasospastic reactions have been reported with therapeutic doses of the ergotamine-containing drugs when coadministered with these antibiotics.

Pregnancy

Teratogenic Effects

Pregnancy Category X:There are no studies on the placental transfer or teratogenicity of Ergomar®. Ergotamine crosses the placenta in small amounts, although it does not appear to be embryotoxic in this quantity. However, prolonged vasoconstriction of the uterine vessels and/or increased myometrial tone leading to reduced myometrial and placental blood flow may have contributed to fetal growth retardation observed in animals. (See CONTRAINDICATIONS)

Nonteratogenic Effects

Ergomar®is contraindicated in pregnancy due to its oxytocic effects of ergotamine (See CONTRAINDICATIONS)

Labor and Delivery

Ergomar®is contraindicated in pregnancy due to its oxytocic effect which is maximal in the third trimester. (See CONTRAINDICATIONS)

Nursing Mothers

Ergot drugs are known to inhibit prolactin but there are no reports of decreased lactation with Ergomar®. Ergotamine is excreted in breast milk and may cause symptoms of vomiting, diarrhea, weak pulse and unstable blood pressure in nursing infants. Because of the potential for serious adverse reactions in nursing infants from Ergomar®, a decision should be made whether to discontinue nursing or discontinue the drug, taking into account the importance of the drug to the mother.

Pediatric Use

Safety and effectiveness in pediatric patients have not been established.

ADVERSE REACTIONS

Cardiovascular:Vasoconstrictive complications of a serious nature may occur at times. These include ischemia, cyanosis, absence of pulse, cold extremities, gangrene, precordial distress and pain, EKG changes and muscle pains. Although these effects occur most commonly with long-term therapy at relatively high doses, they have also been reported with short-term or normal doses. Other cardiovascular adverse effects include transient tachycardia or bradycardia and hypertension.

Gastrointestinal:Nausea and vomiting.

Neurological:paresthesias, numbness, weakness, and vertigo.

Allergic:Localized edema and itching.

Fibrotic Complications:(See WARNINGS).

DRUG ABUSE AND DEPENDENCE

There have been reports of drug abuse and psychological dependence in patients on ergotamine tartrate therapy. Due to the chronicity of vascular headaches, it is imperative that patients be advised not to exceed recommended dosages with long-term use to avoid ergotism. (See PRECAUTIONS)

OVERDOSAGE

Symptoms include vomiting, numbness, tingling, pain and cyanosis of the extremities associated with diminished or absent peripheral pulses; hypertension or hypotension; drowsiness, stupor, coma, convulsions and shock. A case has been reported of reversible bilateral papillitis with ring scotomata in a patient who received five times the recommended daily adult dose over a period of 14 days. Treatment consists of removal of the offending drug. Maintenance of adequate pulmonary ventilation, correction of hypotension, and control of convulsions and blood pressure are important considerations. Treatment of peripheral vasospasm should consist of warmth, but not heat, and protection of the ischemic limbs. Vasodilators may be beneficial but caution must be exercised to avoid aggravating an already existent hypotension.

DOSAGE AND ADMINISTRATION

Procedure

For best results, dosage should start at the first sign of an attack. Early Administration Gives Maximum Effectiveness. At the first sign of an attack or to relieve symptoms after onset of an attack, one 2 mg tablet is placed under the tongue. Another tablet should be taken at half-hour intervals thereafter, if necessary, but dosage must not exceed three tablets in any 24 hour period. Total weekly dosage should not exceed five tablets (10 mg) in any one week. Ergomar®Sublingual Tablets should not be used for chronic daily administration.

HOW SUPPLIED

Ergomar®Sublingual Tablets, 2 mg

(Ergotamine Tartrate Sublingual Tablets USP)

Ergomar® Sublingual Tablets are round, green tablets each containing 2 mg of ergotamine tartrate. They are debossed with the product identification code “LB2” on one side, and are supplied in unit-dose cartons of 20 tablets (10 tablets x 2 cards), NDC 81279-104-20.

STORE AND DISPENSE

Store at 20°- 25°C (68° - 77°F) [see USP Controlled Room Temperature]; excursions permitted to 15° - 30°C (59° - 86°F). Protect from light and heat. Keep out of reach of children.

Manufactured for:

Pangea Pharmaceuticals, LLC
Brielle, NJ 08730, USA

By: Mikart, LLC
Atlanta, GA 30318

©Pangea Pharmaceuticals LLC

All Rights Reserved
Printed in the U.S.A.
Code 1099C00
Rev 08/2024

PRINCIPAL DISPLAY PANEL - 2 mg Tablet Blister Pack Carton

20 Tablets
NDC 81279-104-20

ERGOMAR®

Sublingual Tablets, 2 mg
(Ergotamine Tartrate Sublingual Tablets, USP)
Each tablet contains 2 mg Ergotamine Tartrate, USP

Rx Only

Pangea Pharmaceuticals LLC

3 Tablets

NDC 81279-104-03

ERGOMAR ®

Sublingual Tablets, 2 mg
(Ergotamine Tartrate Sublingual Tablets, USP)

Professional Sample - Not to be Sold

Each tablet contains 2 mg Ergotamine Tartrate, USP

Rx Only

Pangea Pharmaceuticals LLC